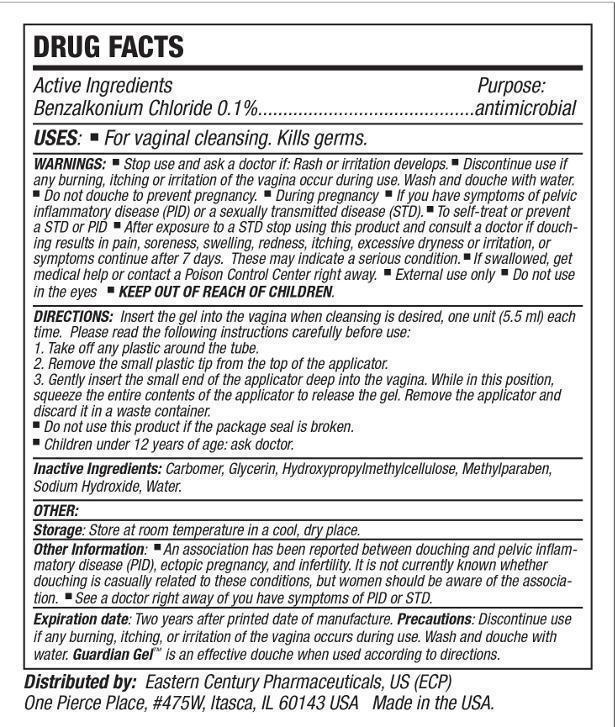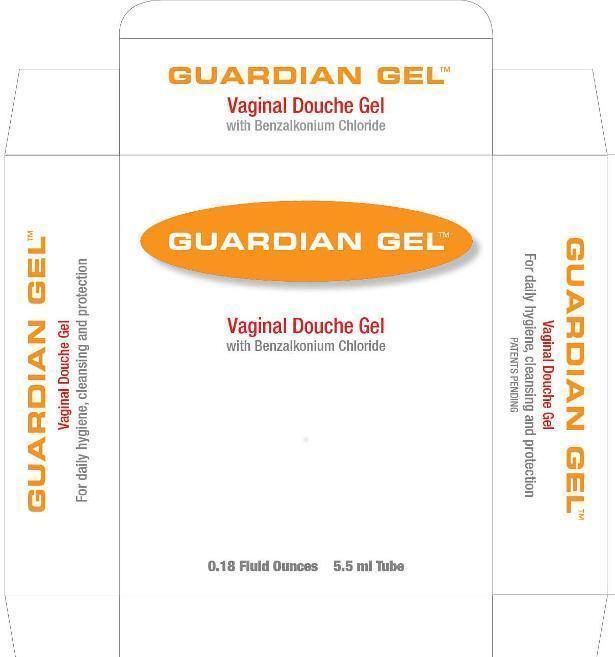 DRUG LABEL: Guardian
NDC: 68915-280 | Form: DOUCHE
Manufacturer: Eastern Century Pharmaceuticals
Category: otc | Type: HUMAN OTC DRUG LABEL
Date: 20240424

ACTIVE INGREDIENTS: BENZALKONIUM CHLORIDE 1 mg/1 mL
INACTIVE INGREDIENTS: CARBOMER 934; GLYCERIN; HYPROMELLOSES; METHYLPARABEN; SODIUM HYDROXIDE; WATER

Eastern Century - Guardian Gel Vaginal Douche

Active ingredient

Benzalkonium Chloride 0.1%

Purpose

antimicrobial

Uses:

- for vaginal cleansing. Kills germs.

Warnings:

Wash and douche with water. Do not Douche to prevent pregnancy. During pregnancy. If you have symptoms of pelvic inflammatory disease (PID) or a sexually transmitted disease (STD). To self-treat or prevent a STD or PID. After exposure to a STD Stop using this product stop using this product and consult a doctor if douching results in pain, soreness, swelling, redness, itching excessive dryness or irritation, or symptoms continue after 7 days. These may indicate serious condition. If swallowed, get medical help or contact a Poison Control Center right away.
External use only.
Do not use in eyes.

Stop use and ask a doctor if:

Rash and irritation and redness develops.

Discontinue use if

any burning, itching, or irritation of the vagina occur during use.

Keep out of reach of children.

Directions:

Insert the gel into the vagina when cleansing is desired, one unit (5.5ml) each time.
Please read the following instructions carefully before use.
1. Take off any plastic around the tube.
2. Remove the small plastic tip from the top of the applicator.
3. Gently insert the small end of the applicator deep into the vagina. While in this position, squeeze the entire contents of the applicator to release the gel. Remove the applicator and discard it in a waste container.

- Do not use this product if the package seal is broken.
- Children under 12 years of age: ask doctor.

Inactive ingredients:

Carbomer, Glycerin, Hydroxypropylmethylcellulose, Methylparaben, Sodium Hydroxide, Water

Storage:

Store at room temperature in a cool, dry place.

Other Information:

An association has been reported between douching and pelvic inflammatory disease (PID), ectopic pregnancy, and infertility. It is not currently known whether douching is casually related to these conditions, but women should be aware of this association. See a doctor right away if you have symptoms of PID or STD.

Expiration Date:

Two years after printed date of manufacture.

Precautions:

Discontinue use if any burning, itching, or irritation of the vagina occurs during use. Wash and douche with water. Guardian GelTM is an effective douche when used according to the directions.

Distributed by:

Eastern Century Pharmaceuticals, US (ECP)
One Pierce Place, #475W, Itasca, IL 60143 USA
Made in the USA

Front Label

Guardian Gel

Vaginal Douche Gel with Benzalkonium Chloride

0.18 fl oz. 5.5 ml